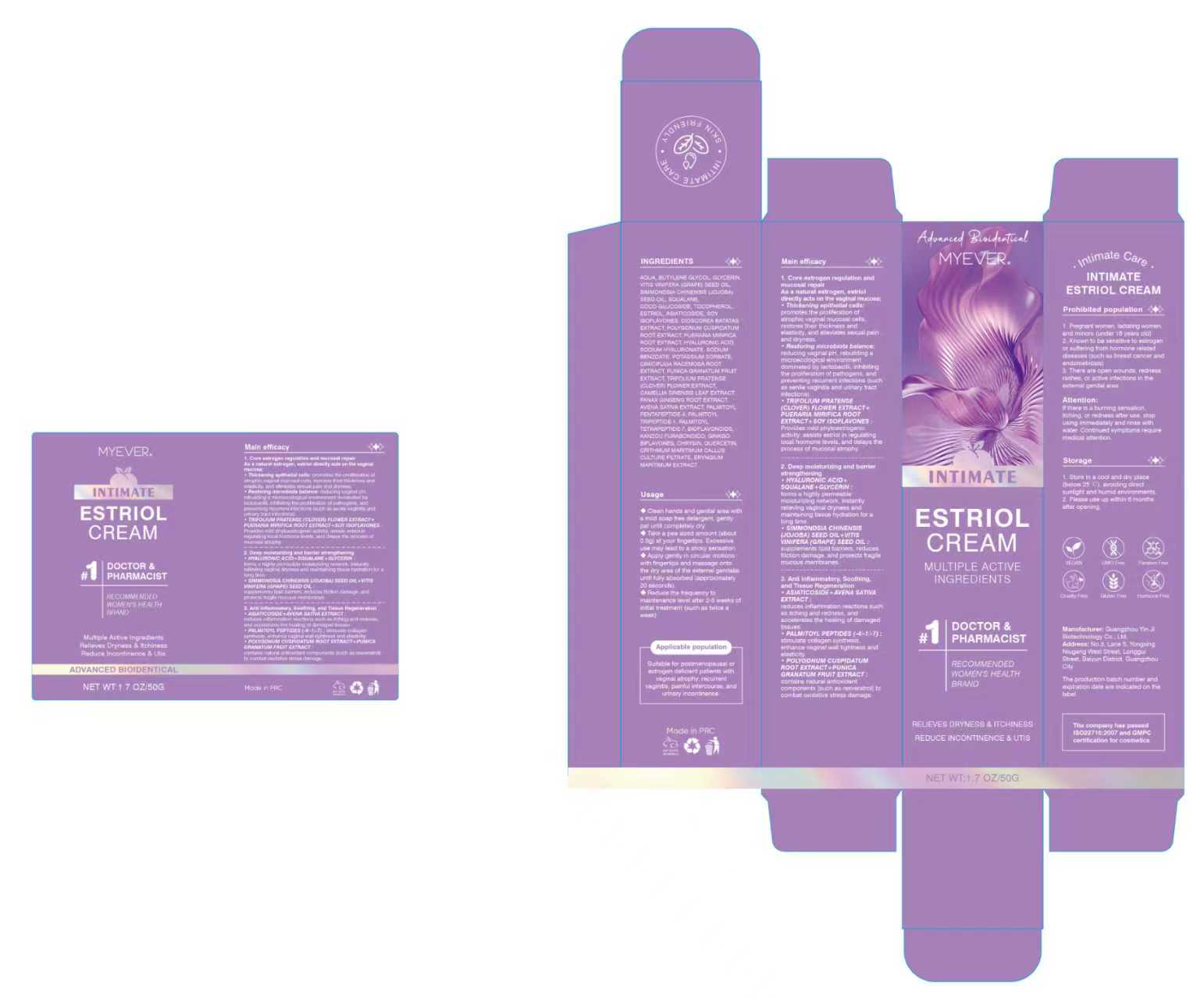 DRUG LABEL: MYEVER
NDC: 87066-5915 | Form: CREAM
Manufacturer: Hubei Redrui Building Materials Co., Ltd.
Category: otc | Type: HUMAN OTC DRUG LABEL
Date: 20250915

ACTIVE INGREDIENTS: ESTRIOL 0.2 g/100 g
INACTIVE INGREDIENTS: AQUA 77.9555 g/100 g; AVENA SATIVA (OAT) KERNEL OIL 0.1 g/100 g; PALMITOYL TRIPEPTIDE-1 0.0015 g/100 g; PALMITOYL TETRAPEPTIDE-7 0.0015 g/100 g; SODIUM BENZOATE 0.15 g/100 g; ERYNGIUM MARITIMUM ROOT 0.1 g/100 g; VITIS VINIFERA (GRAPE) SEED OIL 4 g/100 g; SOY ISOFLAVONES 0.3 g/100 g; CIMICIFUGA RACEMOSA ROOT 0.1 g/100 g; POLYGONUM CUSPIDATUM ROOT 0.35 g/100 g; SIMMONDSIA CHINENSIS (JOJOBA) SEED OIL 2.8 g/100 g; CRITHMUM MARITIMUM 0.1 g/100 g; BUTYLENE GLYCOL 4.5 g/100 g; PUNICA GRANATUM FRUIT JUICE 0.1 g/100 g; MYRICETIN 0.02 g/100 g; DIOSCOREA OPPOSITIFOLIA (WILD YAM) ROOT 0.5 g/100 g; ASIATICOSIDE 0.2 g/100 g; HYALURONIC ACID 0.05 g/100 g; SODIUM HYALURONATE 0.12 g/100 g; PALMITOYL PENTAPEPTIDE-4 0.0015 g/100 g; TOCOPHEROL 0.25 g/100 g; GLABRIDIN 0.02 g/100 g; POTASSIUM SORBATE 0.18 g/100 g; GINKGO BILOBA LEAF 0.05 g/100 g; PUERARIA MONTANA VAR. LOBATA ROOT 0.3 g/100 g; GLYCERIN 3.2 g/100 g; COCO-GLUCOSIDE 1.5 g/100 g; TRIFOLIUM PRATENSE (CLOVER) FLOWER 0.1 g/100 g; PANAX GINSENG ROOT 0.1 g/100 g; SQUALANE 2.5 g/100 g; CAMELLIA SINENSIS LEAF 0.1 g/100 g; CITRUS BIOFLAVONOIDS 0.05 g/100 g

Active ingredient(s)

Estriol 0.2%

Purpose(s)

Skin Protectant

Uses

- Temporarily relieves external vulvar dryness
- Helps prevent and temporarily protects irritated skin.

Warnings

For external use only.

Do not use

- If you are pregnant or breast-feeding.
- On minors under 18 years of age.
- If you have a known sensitivity to estrogen or a hormone-related condition (e.g., breast cancer, endometriosis).
- On open wounds, swollen areas, rashes, or active infections.

When using this product

Avoid contact with eyes.

Stop use and ask a doctor if

- A burning sensation, itching, or redness occurs and persists.
- Condition worsens or symptoms last more than 7 days.

Pregnancy or breast feeding section

Do not use if pregnant or breast-feeding.

Keep out of reach of children

In case of accidental ingestion, get medical help or contact a Poison Control Center right away.

Directions

1. Cleanse hands and the external vulvar area with a mild, soap-free cleanser and pat dry.
2. Apply a pea-sized amount (approx. 0.3 g) to the fingertip.
3. Gently apply and massage into the dry areas of the vulva in a circular motion until fully absorbed.
4. After an initial treatment of 2-3 weeks, reduce frequency to a maintenance level (e.g., twice a week).

Other information

- Store in a cool, dry place below 25°C (77°F).
- Avoid direct sunlight and high humidity.
- Use within 6 months after opening.

Inactive ingredients

AQUA, BUTYLENE GLYCOL, GLYCERIN, VITIS VINIFERA (GRAPE) SEED OIL, SIMMONDSIA CHINENSIS (JOJOBA) SEED OIL, SQUALANE, COCO-GLUCOSIDE, TOCOPHEROL, ASIATICOSIDE, SOY ISOFLAVONES, DIOSCOREA OPPOSITIFOLIA (WILD YAM) ROOT, POLYGONUM CUSPIDATUM ROOT, PUERARIA MONTANA VAR. LOBATA ROOT, HYALURONIC ACID, SODIUM HYALURONATE, SODIUM BENZOATE, POTASSIUM SORBATE, CIMICIFUGA RACEMOSA ROOT, PUNICA GRANATUM FRUIT JUICE, TRIFOLIUM PRATENSE (CLOVER) FLOWER, CAMELLIA SINENSIS LEAF EXTRACT, PANAX GINSENG ROOT, AVENA SATIVA (OAT) KERNEL OIL, PALMITOYL PENTAPEPTIDE-4, PALMITOYL TRIPEPTIDE-1, PALMITOYL TETRAPEPTIDE-7, CITRUS BIOFLAVONOIDS, GLABRIDIN, GINKGO BILOBA LEAF, MYRICETIN, CRITHMUM MARITIMUM, ERYNGIUM MARITIMUM ROOT

Questions or comments?

934-935-7135 / Rangelcervel824@gmail.com

Box Front Panel

MYEVER INTIMATE ESTRIOL CREAM